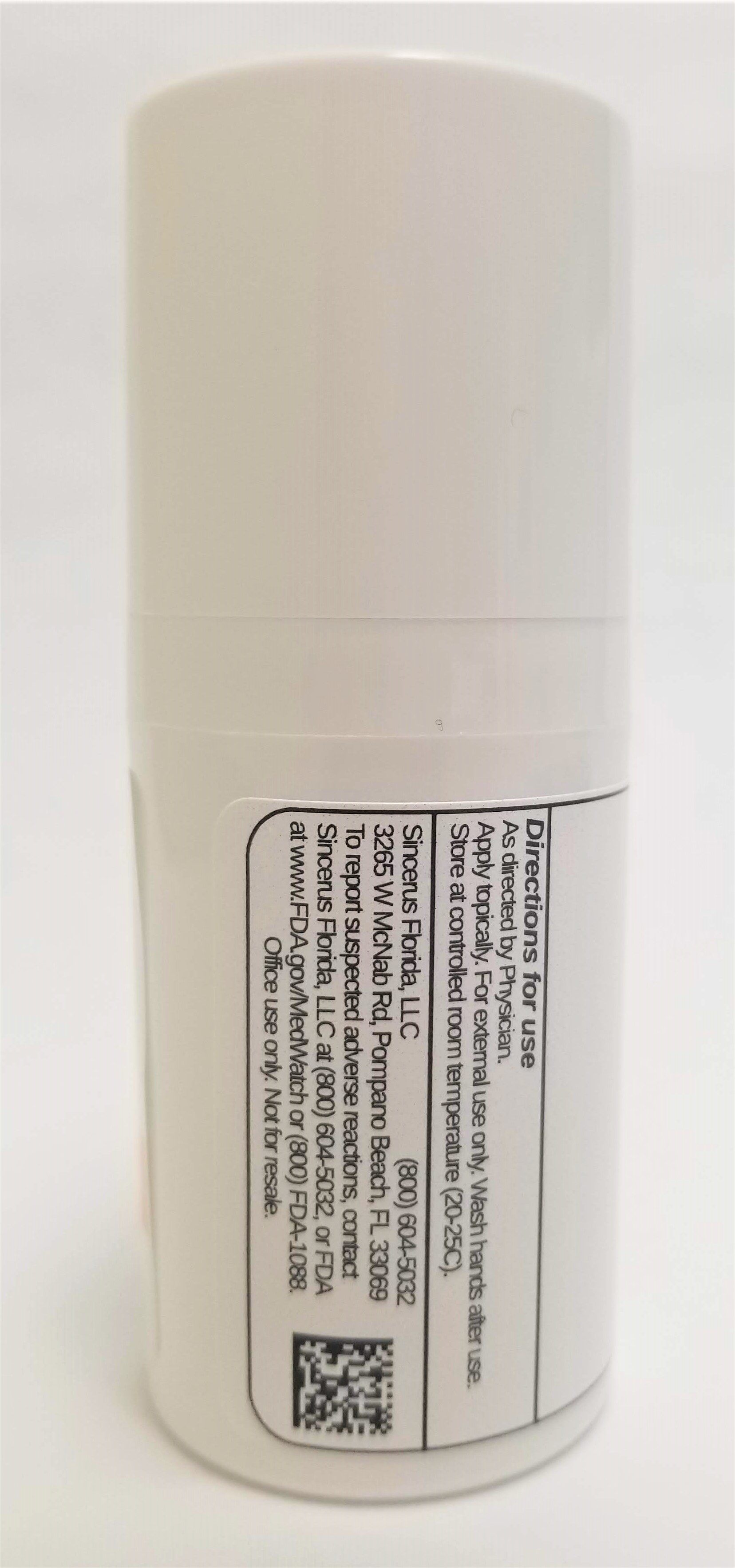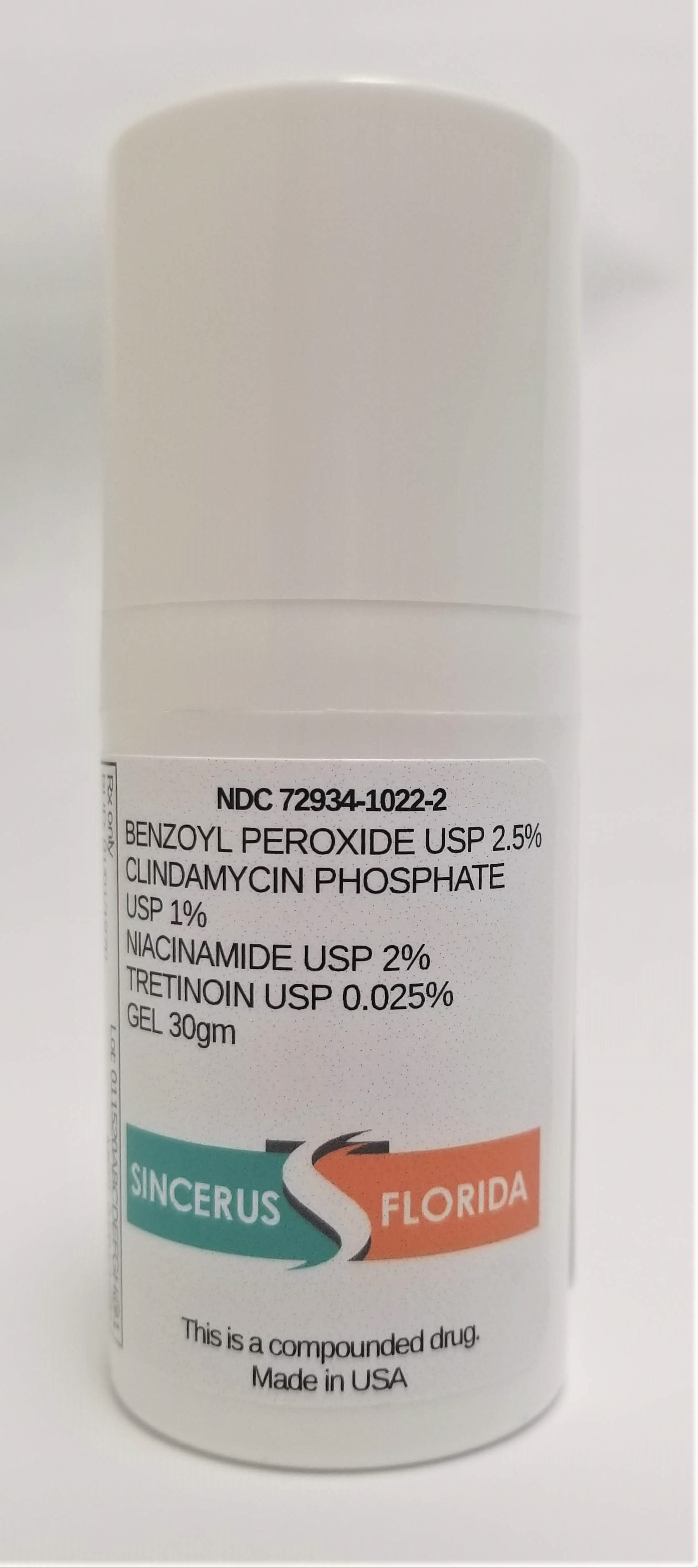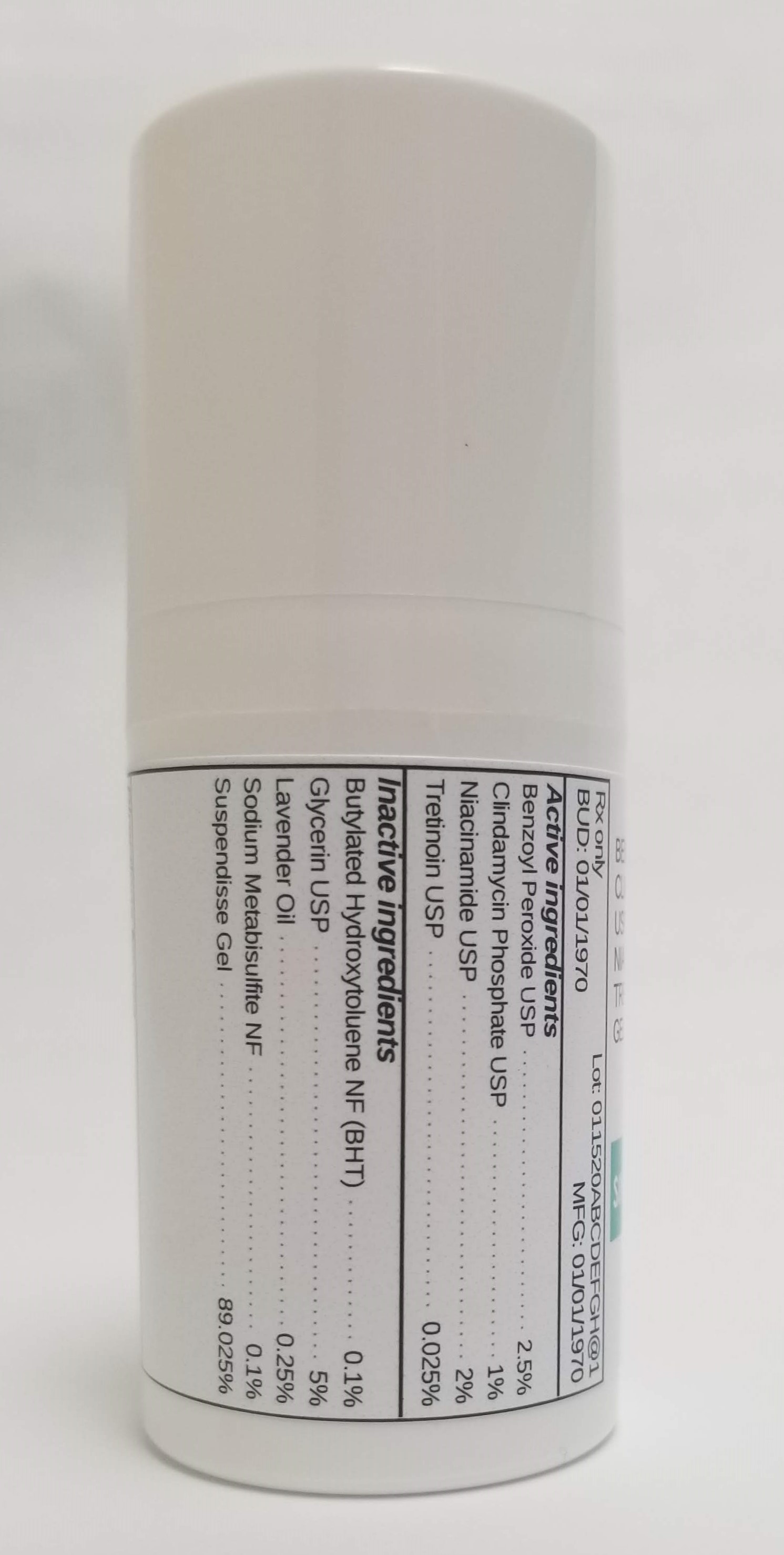 DRUG LABEL: BENZOYL PEROXIDE 2.5% / CLINDAMYCIN 1% / NIACINAMIDE 2% / TRETINOIN 0.025%
NDC: 72934-1022 | Form: GEL
Manufacturer: Sincerus Florida, LLC
Category: prescription | Type: HUMAN PRESCRIPTION DRUG LABEL
Date: 20190522

ACTIVE INGREDIENTS: TRETINOIN 0.025 g/100 g; BENZOYL PEROXIDE 2.5 g/100 g; CLINDAMYCIN PHOSPHATE 1 g/100 g; NIACINAMIDE 2 g/100 g

BENZOYL PEROXIDE 2.5% / CLINDAMYCIN 1% / NIACINAMIDE 2% / TRETINOIN 0.025%